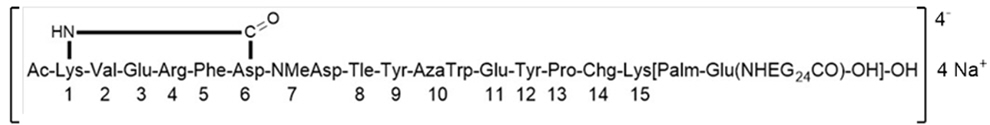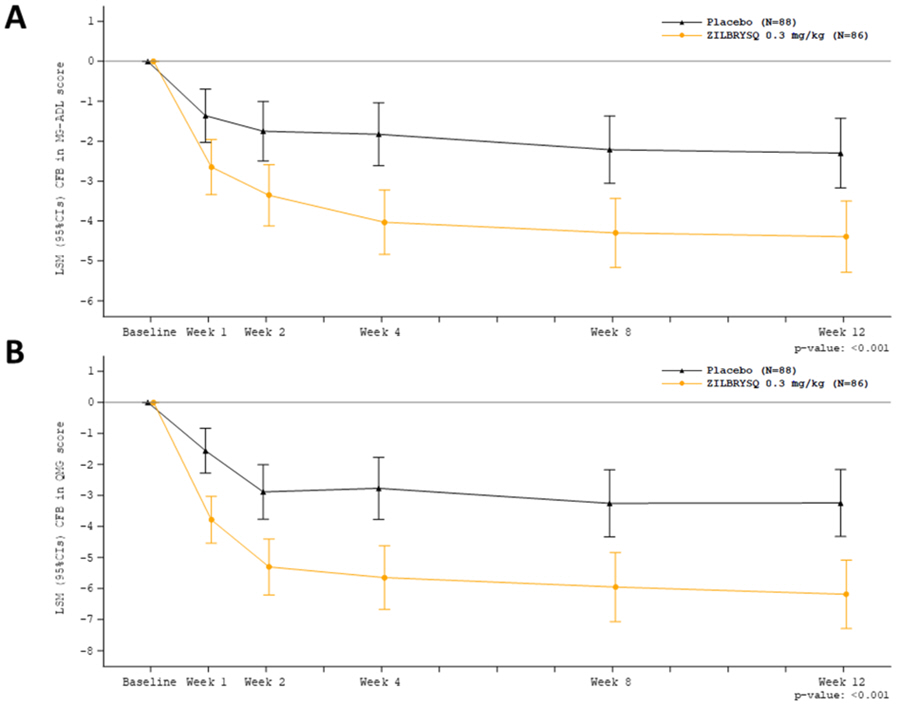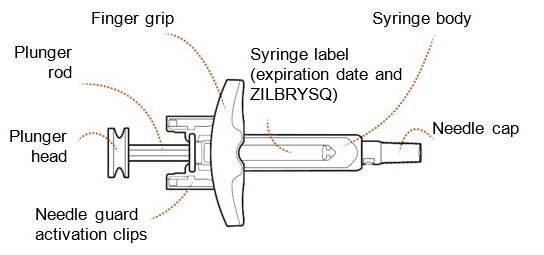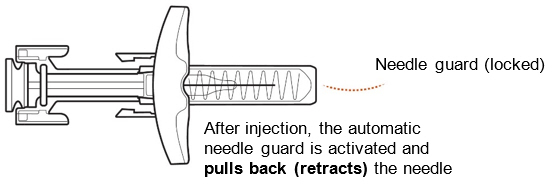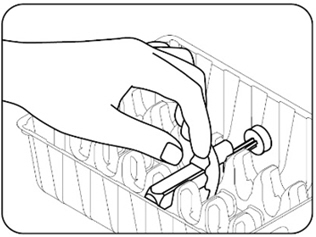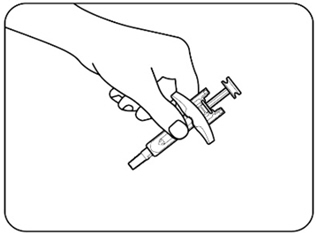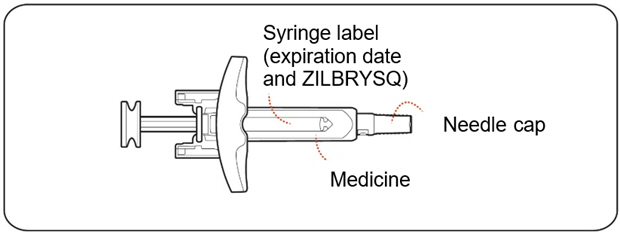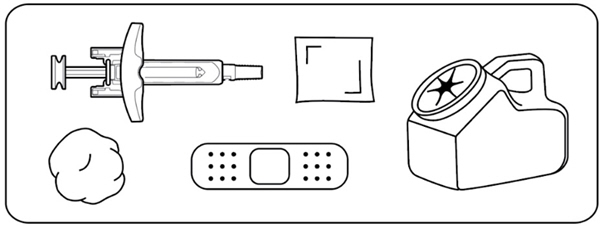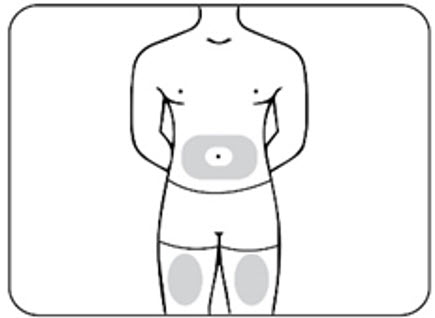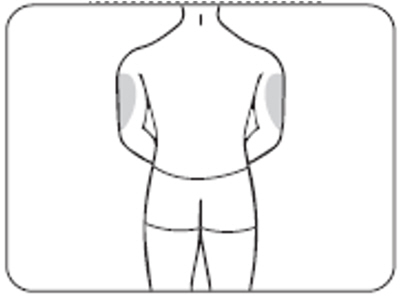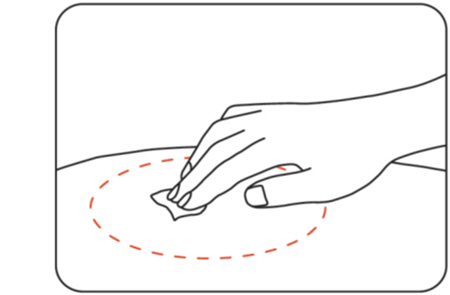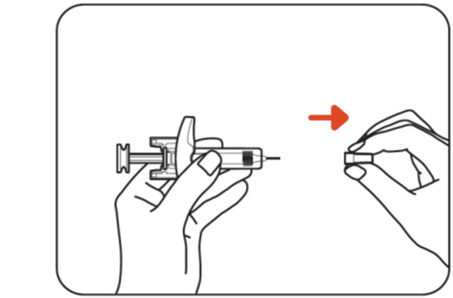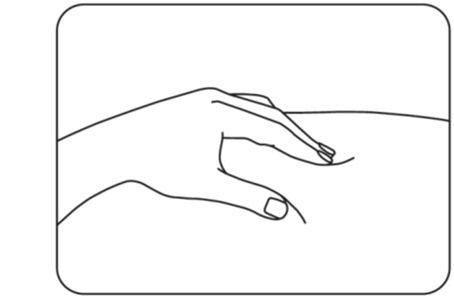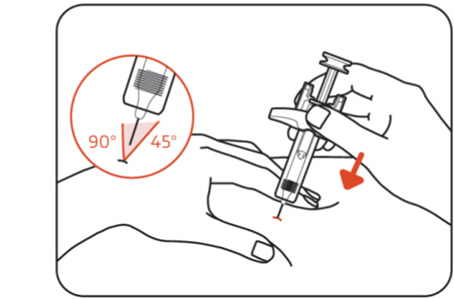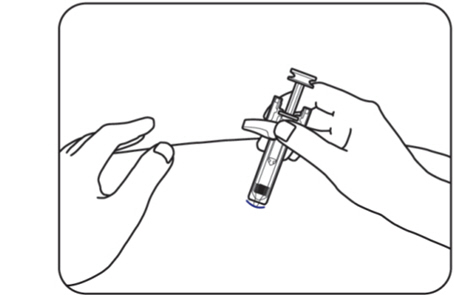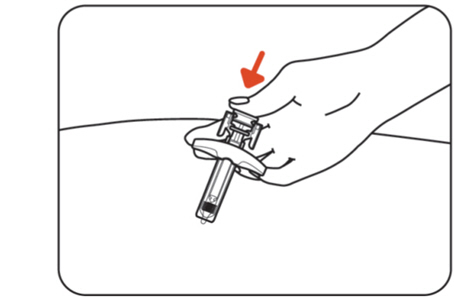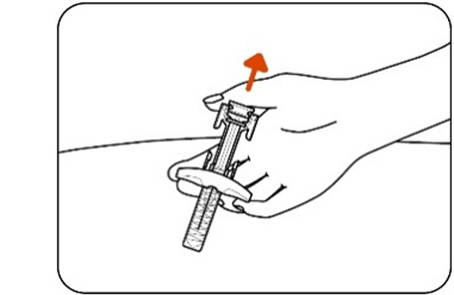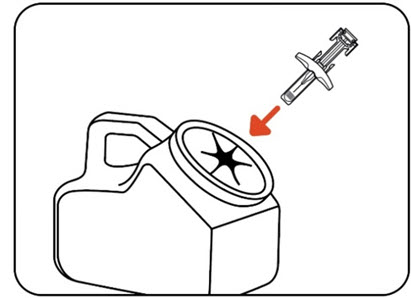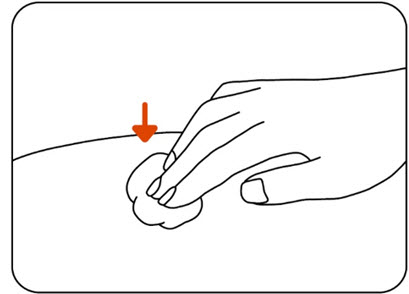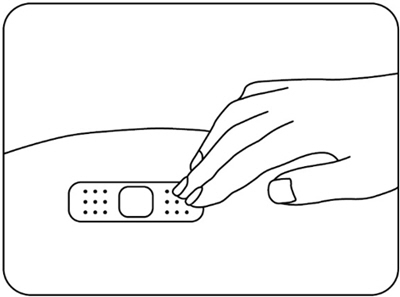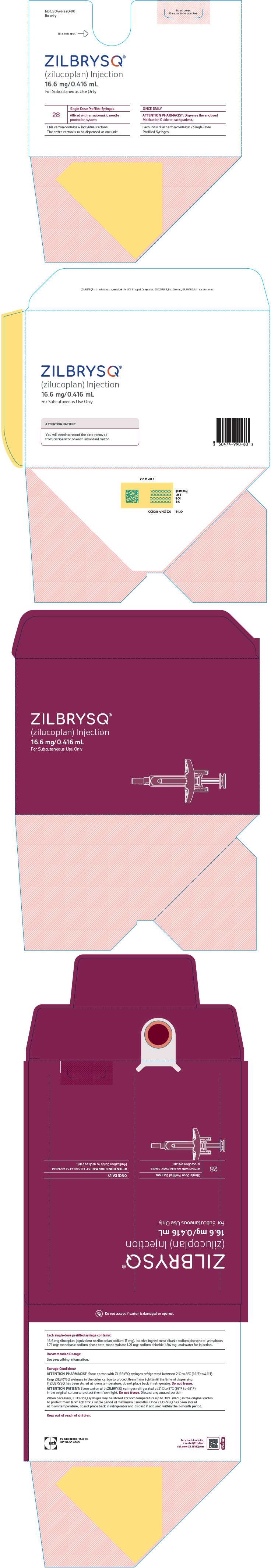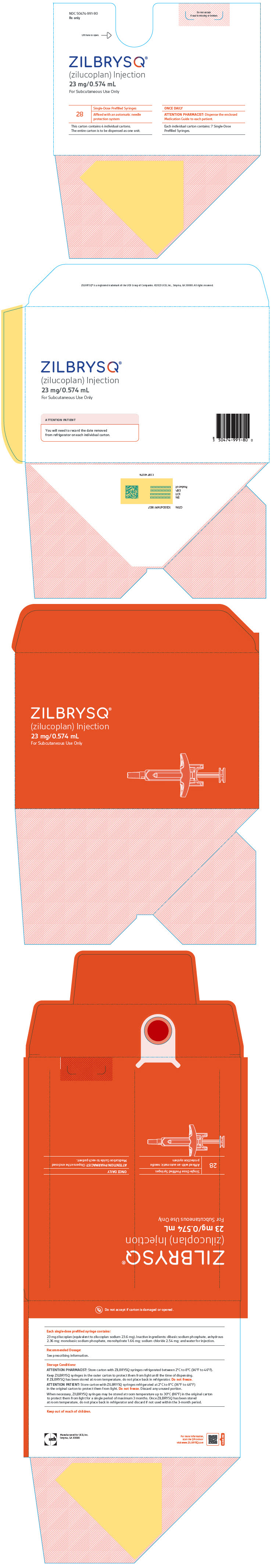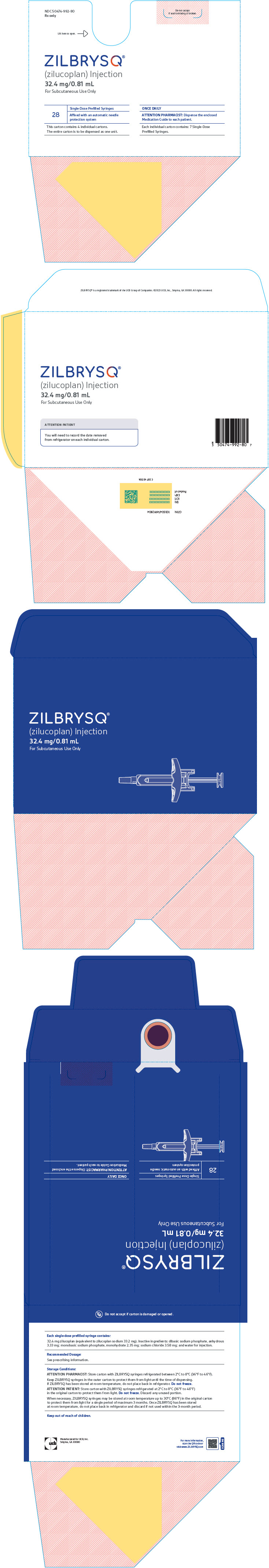 DRUG LABEL: ZILBRYSQ
NDC: 50474-990 | Form: INJECTION, SOLUTION
Manufacturer: UCB, Inc.
Category: prescription | Type: HUMAN PRESCRIPTION DRUG LABEL
Date: 20260203

ACTIVE INGREDIENTS: ZILUCOPLAN 40 mg/1 mL
INACTIVE INGREDIENTS: SODIUM PHOSPHATE, MONOBASIC, MONOHYDRATE 1.21 mg/1 mL; SODIUM PHOSPHATE, DIBASIC, ANHYDROUS 1.71 mg/1 mL; SODIUM CHLORIDE 1.84 mg/1 mL; WATER

HIGHLIGHTS OF PRESCRIBING INFORMATION

These highlights do not include all the information needed to use ZILBRYSQ safely and effectively. See full prescribing information for ZILBRYSQ.
ZILBRYSQ (zilucoplan) injection, for subcutaneous use
Initial U.S. Approval: 2023

WARNING: SERIOUS MENINGOCOCCAL INFECTIONS

See full prescribing information for complete boxed warning.

ZILBRYSQ increases the risk of serious and life-threatening infections caused by Neisseria meningitidis. (5.1)

- Complete or update meningococcal vaccination at least 2 weeks prior to the first dose of ZILBRYSQ, unless the risks of delaying ZILBRYSQ outweigh the risks of developing a serious infection. Comply with the most current Advisory Committee on Immunization Practices (ACIP) recommendations for meningococcal vaccination in patients receiving a complement inhibitor. (5.1)
- Patients receiving ZILBRYSQ are at increased risk for invasive disease caused by N. meningitidis, even if they develop antibodies following vaccination. Monitor patients for early signs and symptoms of meningococcal infections and evaluate immediately if infection is suspected. (5.1)

ZILBRYSQ is available only through a restricted program called ZILBRYSQ REMS. (5.2)

RECENT MAJOR CHANGES

Boxed Warning | 2/2025
Dosage and Administration (2.1) | 2/2025
Contraindications (4) | 2/2025
Warnings and Precautions (5.1, 5.2, 5.3) | 2/2025

1 INDICATIONS AND USAGE

ZILBRYSQ is a complement inhibitor indicated for the treatment of generalized myasthenia gravis (gMG) in adult patients who are anti-acetylcholine receptor (AChR) antibody positive. (1)

2 DOSAGE AND ADMINISTRATION

- Obtain baseline amylase and lipase. (2.2)
- For subcutaneous injection only. (2.3)
- Recommended dosage (2.3):
  Body Weight | Once Daily Dosage | Plunger Rod Color of Prefilled Syringe
  Less than 56 kg | 16.6 mg | RUBINE RED
  56 kg to less than 77 kg | 23 mg | ORANGE
  77 kg and above | 32.4 mg | DARK BLUE
- See Full Prescribing Information for instructions on dosage, preparation, and administration. (2.4, 2.5)

3 DOSAGE FORMS AND STRENGTHS

Injection: 16.6 mg/0.416 mL, 23 mg/0.574 mL, or 32.4 mg/0.81 mL zilucoplan in single-dose prefilled syringes. (3)

4 CONTRAINDICATIONS

ZILBRYSQ is contraindicated for initiation in patients with unresolved serious Neisseria meningitidisinfection. (4)

5 WARNINGS AND PRECAUTIONS

- Other Infections: Use caution when administering ZILBRYSQ to patients with any other systemic infection. (5.3)
- Pancreatitis and pancreatic cysts have been reported in patients treated with ZILBRYSQ. Discontinue ZILBRYSQ in patients with suspected pancreatitis and initiate appropriate management until pancreatitis is ruled out or has resolved. (5.4)

6 ADVERSE REACTIONS

The most common adverse reactions (≥10%) in patients with gMG were injection site reactions, upper respiratory tract infection, and diarrhea. (6.1)

To report SUSPECTED ADVERSE REACTIONS, contact UCB, Inc. at 844-599-2273 or FDA at 1-800-FDA-1088 or www.fda.gov/medwatch.

8 USE IN SPECIFIC POPULATIONS

Pregnancy: Based on animal data, may cause fetal harm. (8.1)

FULL PRESCRIBING INFORMATION

WARNING: SERIOUS MENINGOCOCCAL INFECTIONS

ZILBRYSQ, a complement inhibitor, increases the risk of serious infections caused by Neisseria meningitidis [see Warnings and Precautions (5.1)] . Life-threatening and fatal meningococcal infections have occurred in patients treated with complement inhibitors. These infections may become rapidly life-threatening or fatal if not recognized and treated early.

- Complete or update vaccination for meningococcal bacteria (for serogroups A, C, W, Y, and B) at least 2 weeks prior to the first dose of ZILBRYSQ, unless the risks of delaying therapy outweigh the risk of developing a serious infection. Comply with the most current Advisory Committee on Immunization Practices (ACIP) recommendations for vaccination against meningococcal bacteria in patients receiving a complement inhibitor. See Warnings and Precautions (5.1)for additional guidance on the management of the risk of serious infections caused by meningococcal bacteria.
- Patients receiving ZILBRYSQ are at increased risk for invasive disease caused by Neisseria meningitidis, even if they develop antibodies following vaccination. Monitor patients for early signs and symptoms of serious meningococcal infections and evaluate immediately if infection is suspected.

Because of the risk of serious meningococcal infections, ZILBRYSQ is available only through a restricted program under a Risk Evaluation and Mitigation Strategy (REMS) called ZILBRYSQ REMS [see Warnings and Precautions (5.2)] .

1 INDICATIONS AND USAGE

ZILBRYSQ is indicated for the treatment of generalized myasthenia gravis (gMG) in adult patients who are anti-acetylcholine receptor (AChR) antibody positive.

2 DOSAGE AND ADMINISTRATION

2.1 Recommended Vaccination and Prophylaxis for Meningococcal Infection

Vaccinate patients against meningococcal infection (serogroups A, C, W, Y, and B) according to current ACIP recommendations at least 2 weeks prior to initiation of ZILBRYSQ [see Warnings and Precautions (5.1)] .

If urgent ZILBRYSQ therapy is indicated in a patient who is not up to date with meningococcal vaccines according to ACIP recommendations, provide the patient with antibacterial drug prophylaxis and administer these vaccines as soon as possible [see Warnings and Precautions (5.1)] .

Healthcare providers who prescribe ZILBRYSQ must enroll in the ZILBRYSQ REMS [see Warnings and Precautions (5.2)] .

2.2 Recommended Testing Before Initiating ZILBRYSQ

Before initiating ZILBRYSQ, obtain baseline lipase and amylase levels [see Warnings and Precautions (5.4)] .

2.3 Recommended Dosage

The recommended dosage of ZILBRYSQ is given once daily as a subcutaneous injection and is dependent on actual body weight (see Table 1).

Table 1: Total Daily Dosage by Body Weight Range
Body Weight | Once Daily Dosage | Plunger Rod Color of Prefilled Syringe
Less than 56 kg | 16.6 mg | RUBINE RED
56 kg to less than 77 kg | 23 mg | ORANGE
77 kg and above | 32.4 mg | DARK BLUE

2.4 Preparation Instructions

- ZILBRYSQ prefilled syringes can be stored in a refrigerator in the original carton. ZILBRYSQ can also be stored at room temperature in the original carton for up to 3 months or until the expiration date, whichever occurs first.
  If stored in the refrigerator:
  - Before injecting, take 1 ZILBRYSQ prefilled syringe out of the refrigerator and place it on a clean, flat surface. Allow ZILBRYSQ to reach room temperature out of direct sunlight (30 to 45 minutes). Do not heat or place in microwave.
  - Immediately return the carton with the other prefilled syringes to the refrigerator.
  If stored at room temperature:
  - Remove 1 ZILBRYSQ prefilled syringe from the carton.
  - Do not return ZILBRYSQ to the refrigerator after it has been stored at room temperature.
- Visually inspect ZILBRYSQ for particulate matter and discoloration prior to administration. ZILBRYSQ is a clear to slightly opalescent, colorless solution. Do not use if the solution contains visible particles, is cloudy, or if foreign particulate matter is present. ZILBRYSQ does not contain preservatives; unused portions of drug remaining in the syringe should be discarded.
- Each prefilled syringe is single-dose only.

2.5 Administration Instructions

- ZILBRYSQ is intended for use under the guidance and supervision of a healthcare professional. Patients may self-inject ZILBRYSQ after training in subcutaneous injection technique. Provide proper training to patients and/or caregivers on the subcutaneous injection technique of ZILBRYSQ according to the "Instructions for Use" [see Instructions for Use] .
- Administer ZILBRYSQ subcutaneously into areas of the abdomen, thighs, or back of the upper arms that are not tender, bruised, red, or hard. Avoid injecting into areas with scars or stretch marks. Rotate injection sites for each administration. Administration of ZILBRYSQ in the upper, outer arm should be performed by a caregiver.
- When using ZILBRYSQ prefilled syringes, inject the full contents of the single-dose prefilled syringe.
- Discard ZILBRYSQ prefilled syringe after use. Do not reuse.
- Instruct the patient that the daily dose should be administered at approximately the same time each day.
- If a dose is missed, administer the dose as soon as possible. Thereafter, resume dosing at the regular scheduled time. Do not administer more than 1 dose per day.

3 DOSAGE FORMS AND STRENGTHS

Injection: 16.6 mg/0.416 mL, 23 mg/0.574 mL, or 32.4 mg/0.81 mL of zilucoplan as a clear to slightly opalescent, colorless solution in single-dose prefilled syringes.

4 CONTRAINDICATIONS

ZILBRYSQ is contraindicated for initiation in patients with unresolved serious Neisseria meningitidisinfection [see Warnings and Precautions (5.1)] .

5 WARNINGS AND PRECAUTIONS

5.1 Serious Meningococcal Infections

ZILBRYSQ, a complement inhibitor, increases a patient's susceptibility to serious, life-threatening, or fatal infections caused by meningococcal bacteria (septicemia and/or meningitis) in any serogroup, including non-groupable strains. Life-threatening and fatal meningococcal infections have occurred in both vaccinated and unvaccinated patients treated with complement inhibitors. The initiation of ZILBRYSQ treatment is contraindicated in patients with unresolved serious Neisseria meningitidisinfection.

Complete or update meningococcal vaccination (for serogroups A, C, W, Y and B) at least 2 weeks prior to administration of the first dose of ZILBRYSQ, according to current ACIP recommendations for patients receiving a complement inhibitor. Revaccinate patients in accordance with ACIP recommendations considering the duration of ZILBRYSQ therapy. Note that ACIP recommends an administration schedule in patients receiving complement inhibitors that differs from the administration schedule in the vaccine prescribing information.

If urgent ZILBRYSQ therapy is indicated in a patient who is not up to date with meningococcal vaccines according to ACIP recommendations, provide the patient with antibacterial drug prophylaxis and administer meningococcal vaccines as soon as possible. Various durations and regimens of antibacterial drug prophylaxis have been considered, but the optimal durations and drug regimens for prophylaxis and their efficacy have not been studied in unvaccinated or vaccinated patients receiving complement inhibitors, including ZILBRYSQ. The benefits and risks of treatment with ZILBRYSQ, as well as the benefits and risks of antibacterial drug prophylaxis in unvaccinated or vaccinated patients, must be considered against the known risks for serious infections caused by Neisseria meningitidis.

Vaccination does not eliminate the risk of meningococcal infections, despite development of antibodies following vaccination.

Closely monitor patients for early signs and symptoms of meningococcal infection and evaluate patients immediately if infection is suspected. Inform patients of these signs and symptoms and instruct patients to seek immediate medical care if these signs and symptoms occur. Promptly treat known infections. Meningococcal infection may become rapidly life-threatening or fatal if not recognized and treated early. Consider interruption of ZILBRYSQ in patients who are undergoing treatment for serious meningococcal infection, depending on the risks of interrupting treatment in the disease being treated [ see Contraindications (4)] .

ZILBRYSQ is available only through a restricted program under a Risk Evaluation and Mitigation Strategy (REMS) [see Warnings and Precautions (5.2)] .

5.2 ZILBRYSQ REMS

ZILBRYSQ is available only through a restricted program under a REMS called ZILBRYSQ REMS, because of the risk of serious meningococcal infections [see Warnings and Precautions (5.1)] .

Notable requirements of the ZILBRYSQ REMS include the following:

- Prescribers must enroll in the REMS.
- Prescribers must counsel patients about the risk of serious meningococcal infection.
- Prescribers must provide the patients with the REMS educational materials.
- Prescribers must assess patient vaccination status for meningococcal vaccines (against serogroups A, C, W, Y, and B) and vaccinate if needed according to current ACIP recommendations two weeks prior to the first dose of ZILBRYSQ.
- Prescribers must provide a prescription for antibacterial drug prophylaxis if treatment must be started urgently and the patient is not up to date with meningococcal vaccines according to current ACIP recommendations at least two weeks prior to the first dose of ZILBRYSQ.
- Pharmacies that dispense ZILBRYSQ must be certified in the REMS and must verify prescribers are certified.
- Patients must receive counseling from the prescriber about the need to receive meningococcal vaccines per ACIP recommendations, the need to take antibiotics as directed by the prescriber, and the signs and symptoms of meningococcal infection.
- Patients must be instructed to carry the Patient Safety Card with them at all times during and for 2 months following treatment discontinuation with ZILBRYSQ.

Further information is available at www.ZILBRYSQREMS.com or 1-877-414-8353.

5.3 Other Infections

Serious infections with Neisseriaspecies (other than Neisseria meningitidis), including disseminated gonococcal infections, have been reported in patients treated with complement inhibitors.

ZILBRYSQ blocks terminal complement activation; therefore, patients may have increased susceptibility to infections, especially with encapsulated bacteria, such as infections caused by Neisseria meningitidisbut also Streptococcus pneumoniae, Haemophilus influenzae, and to a lesser extent, Neisseria gonorrhoeae. Administer vaccinations for the prevention of Streptococcus pneumoniaeinfection according to ACIP recommendations. Patients receiving ZILBRYSQ are at increased risk for infections due to these organisms, even if they develop antibodies following vaccination.

5.4 Pancreatitis and Other Pancreatic Conditions

Pancreatitis and pancreatic cysts have been reported in patients treated with ZILBRYSQ.

During the open-label extension studies, seven (3.3%) patients experienced pancreatic events, including 4 (1.9%) patients with pancreatitis and 3 (1.4%) with pancreatic cysts.

In the 3-month, double-blind Study 1, adverse reactions of increased lipase were reported in six (6.9%) patients treated with ZILBRYSQ compared to no patients on placebo, and adverse reactions of increased amylase were reported in four (4.7%) patients treated with ZILBRYSQ compared to one (1.1%) patient on placebo. Lipase levels exceeded three times the upper limit of normal in six (7%) patients after being started on ZILBRYSQ compared to no patients on placebo.

Patients should be informed of this risk before starting ZILBRYSQ. Obtain lipase and amylase levels at baseline before starting treatment with ZILBRYSQ. Discontinue ZILBRYSQ in patients with suspected pancreatitis and initiate appropriate management until pancreatitis is ruled out or has resolved.

6 ADVERSE REACTIONS

The following clinically significant adverse reactions are discussed in greater detail in other sections of the labeling:

- Serious Meningococcal Infections [see Warnings and Precautions (5.1)]
- Other Infections [see Warnings and Precautions (5.3)]
- Pancreatitis and Other Pancreatic Conditions [see Warnings and Precautions (5.4)]

6.1 Clinical Trials Experience

Because clinical trials are conducted under widely varying conditions, adverse reaction rates observed in the clinical trials of a drug cannot be directly compared to rates in the clinical trials of another drug and may not reflect the rates observed in practice.

A total of 212 patients were treated with ZILBRYSQ 0.3 mg/kg in clinical studies in gMG. Of these, 137 patients were exposed for at least 6 months, and 87 were exposed for at least 1 year.

In a placebo-controlled study (Study 1) in patients with gMG, 86 patients received ZILBRYSQ 0.3 mg/kg [see Clinical Studies (14)] . Of these 86 patients, approximately 61% were female, 77% were White, 8% were Asian, and 8% were of Hispanic or Latino ethnicity. The mean age at study entry was 52.6 years (range 21 to 75 years). Table 2 summarizes the adverse reactions reported in at least 5% of patients treated with ZILBRYSQ and more frequently than placebo. The most common adverse reactions (reported in at least 10% of patients treated with ZILBRYSQ) were injection site reactions, upper respiratory tract infections, and diarrhea.

Table 2: Adverse Reactions in at least 5% of Patients Treated with ZILBRYSQ and More Frequently than in Patients who Received Placebo in Study 1
Adverse Reaction | ZILBRYSQ 0.3 mg/kg (n=86) % | Placebo (n=88) %
Injection site reactions | 29 | 16
Upper respiratory tract infections | 14 | 7
Diarrhea | 11 | 2
Urinary tract infection | 8 | 5
Nausea or vomiting | 8 | 7
Lipase increased | 7 | 0
Amylase increased | 5 | 1

Pancreatic Events

In addition to increases in amylase and lipase observed in Study 1, pancreatic events, including pancreatitis and pancreatic cysts have been observed in patients taking ZILBRYSQ [see Warnings and Precautions (5.4)] .

Adverse Laboratory Changes in Clinical Trials

Additional laboratory abnormalities included transient elevations of blood eosinophils, which were of uncertain clinical significance.

6.2 Postmarketing Experience

Adverse Reactions from Observational Studies

Morphea

In the open-label extension studies, which included 213 patients, morphea was observed in 10 (5%) patients; most cases had a time to onset longer than one year after start of treatment and were mild to moderate in severity. One patient discontinued ZILBRYSQ because of morphea.

8 USE IN SPECIFIC POPULATIONS

8.1 Pregnancy

Pregnancy Exposure Registry

There is a pregnancy exposure registry that monitors pregnancy outcomes in women exposed to ZILBRYSQ during pregnancy. Patients or healthcare providers may contact UCBCares at 1-844-599-CARE (2273) or email ucbcares@ucb.com, so that information about the exposure of ZILBRYSQ during pregnancy and/or breastfeeding can be collected.

Risk Summary

There are no available data on ZILBRYSQ use in pregnant women to evaluate for a drug-associated risk of major birth defects, miscarriage, or other adverse maternal or fetal outcomes. Administration of zilucoplan to pregnant monkeys resulted in increases in embryofetal death at maternal exposures similar to those in humans at therapeutic doses (see Animal Data) .

All pregnancies have a background risk of birth defect, loss, or other adverse outcomes. The background rate of major birth defects and miscarriage in the indicated population is unknown. In the U.S. general population, the estimated background risk of major birth defects and miscarriage in clinically recognized pregnancies is 2% to 4% and 15% to 20%, respectively.

Data

Animal Data

Subcutaneous administration of zilucoplan (0, 1, 2, or 4 mg/kg/day) to pregnant monkeys throughout gestation resulted in an increase in embryofetal death at all doses, in the absence of maternal toxicity. A no effect dose for adverse developmental effects in monkeys was not identified. The lowest dose tested was associated with maternal exposures (AUC) similar to that in humans at the maximum recommended human dose of 32.4 mg/day.

Data from an ex vivohuman placental transfer model demonstrated transfer of zilucoplan into the fetal compartment at a rate of 0.5% at a steady state plasma concentration of 10 µg/mL zilucoplan, which corresponds to a therapeutic dose of 0.3 mg/kg. The clinical significance of these data in human pregnancies is unknown.

8.2 Lactation

Risk Summary

There are no data on the presence of zilucoplan in human milk, the effects on the breastfed infant, or the effects on milk production. The developmental and health benefits of breastfeeding should be considered along with the mother's clinical need for ZILBRYSQ and any potential adverse effects on the breastfed infant from ZILBRYSQ or from the underlying maternal condition.

8.4 Pediatric Use

Safety and effectiveness in pediatric patients have not been established.

8.5 Geriatric Use

Clinical studies of ZILBRYSQ did not include sufficient numbers of patients aged 65 and older to determine whether they respond differently from younger adult patients.

11 DESCRIPTION

Zilucoplan, a complement inhibitor, is a 15 amino-acid, synthetic macrocyclic peptide.

The molecular formula of zilucoplan is C172H278N24O55in free acid form and its molecular weight is 3562.23 Daltons (free acid form).

The chemical name for zilucoplan sodium is: acetyl‐[L-lysyl^1-L-valyl^2-L-glutamyl^3-L-arginyl^4-L phenylalanyl^5-L aspartyl^6]- N-methyl L-aspartyl^7-L tert-leucyl^8-L tyrosyl^9-L-7-azatryptophyl^10-L glutamyl^11-L-tyrosyl^12-L prolyl^13-L cyclohexylglycyl^14-[L-lysyl^15, Nε-palmitoyl-γ-L-glutamyl-(1-amino-3,6,9,12,15,18,21,24,27,30,33,36,39,42,45,48,51,54,57,60,63,66,69,72-tetracosaoxapentaheptacontan-75-oyl)], cyclic (Lactam 1-6), tetra sodium.

The primary structure for zilucoplan sodium is shown below:

ZILBRYSQ injection is a sterile, clear to slightly opalescent, colorless, preservative-free, buffered solution of zilucoplan (as zilucoplan sodium) for subcutaneous injection, in single-dose prefilled syringes. The solution pH is between 6.5 and 7.5. ZILBRYSQ is supplied in three dose strengths containing 16.6 mg /0.416 mL, 23 mg /0.574 mL, and 32.4 mg/0.81 mL of zilucoplan free acid equivalent to 17 mg, 23.6 mg, and 33.2 mg of zilucoplan sodium, respectively. Additionally, each mL of the solution contains dibasic sodium phosphate, anhydrous (4.11 mg); monobasic sodium phosphate, monohydrate (2.9 mg); sodium chloride (4.42 mg); and water for injection.

12 CLINICAL PHARMACOLOGY

12.1 Mechanism of Action

Zilucoplan binds to the complement protein C5 and inhibits its cleavage to C5a and C5b, preventing the generation of the terminal complement complex, C5b-9.

The precise mechanism by which zilucoplan exerts its therapeutic effect in generalized myasthenia gravis is unknown but is presumed to involve reduction of C5b-9 deposition at the neuromuscular junction.

12.2 Pharmacodynamics

In a placebo-controlled Phase 2 study, patients received zilucoplan 0.3 mg/kg or 0.1 mg/kg for 12 weeks. There was a dose dependent inhibition of complement. Complement inhibition as represented by inhibition of sheep red blood cell (sRBC) lysis was 89.1% within 3 hours after the first administration and 94.9% after the 12-week treatment period in patients receiving ZILBRYSQ 0.3 mg/kg.

In Study 1 [see Clinical Studies (14)], complement inhibition of 97.5% was observed by the end of the first week and sustained throughout the 12-week treatment period for gMG patients treated with the recommended dosage regimen of ZILBRYSQ.

Cardiac Electrophysiology

At a dose two times the maximum approved recommended dose, ZILBRYSQ does not cause clinically significant QTc interval prolongation.

12.3 Pharmacokinetics

The population pharmacokinetics (PK) analysis showed that zilucoplan PK was not time dependent. Following single daily subcutaneous administration of ZILBRYSQ (0.05 mg/kg, 0.1 mg/kg, 0.2 mg/kg, and 0.4 mg/kg) in healthy subjects, increase in peak plasma concentration was approximately dose proportional and increase in area under the curve was less than dose proportional.

Absorption

Following single and multiple daily subcutaneous administration of ZILBRYSQ 0.3 mg/kg in healthy subjects, zilucoplan reached peak plasma concentration generally between 3 to 6 hours post-dose. Following daily subcutaneous dosing of ZILBRYSQ 0.3 mg/kg for 14 days in healthy subjects, both the peak plasma concentration and exposure (AUCtau) increased by approximately 3-fold.

In Study 1 [see Clinical Studies (14)] , after daily repeated subcutaneous administration of ZILBRYSQ 0.3 mg/kg, plasma concentrations of zilucoplan were consistent, with steady state trough concentrations being reached by four weeks of treatment with ZILBRYSQ through twelve weeks.

Distribution

The mean volume of distribution at steady state was 3.51 L in the population pharmacokinetics analysis for adult patients with gMG. Zilucoplan and its 2 major metabolites are highly bound to plasma proteins (>99%).

Elimination

The mean plasma terminal half-life of zilucoplan was approximately 172 hours (7 to 8 days).

Metabolism

As a peptide, ZILBRYSQ is expected to be degraded into small peptides and amino acids via catabolic pathways.

In plasma, two major metabolites, RA103488 and RA102758, were detected. The metabolite RA103488, formed mainly because of cytochrome CYP450 4F2, has pharmacological activity similar to zilucoplan but is present at a much lower concentration compared to zilucoplan. The metabolite RA102758, formed by protease mediated degradation, is pharmacologically inactive. The AUCs of both metabolites were approximately 10% of the parent AUC. The contribution of RA103488 to pharmacological activity is therefore expected to be low.

Excretion

Excretion of zilucoplan and its metabolite in urine and feces was negligible (<1% of the dose).

Specific Populations

Age, Sex, and Race

A population pharmacokinetics analysis assessing the effects of age, sex, and race did not suggest any clinically significant impact of these covariates on zilucoplan exposures.

Patients with Renal Impairment

A dedicated clinical study compared the pharmacokinetics of a single subcutaneous dose of ZILBRYSQ 0.3 mg/kg in subjects with severe renal impairment (as defined by a creatinine clearance <30 mL/min estimated by Cockcroft-Gault formula) to that of matched healthy subjects with normal renal function. A decrease in zilucoplan exposure (AUC0-inf) of 13% was observed. This change in zilucoplan exposures is not expected to be clinically significant. No dose adjustment is required in patients with renal impairment.

Patients with Hepatic Impairment

A dedicated clinical study compared the pharmacokinetics of a single subcutaneous dose of ZILBRYSQ 0.3 mg/kg in subjects with moderate hepatic impairment (as indicated by a Child-Pugh category of moderate [score of 7 to 9]) to that of matched healthy subjects with normal hepatic function. A decrease in zilucoplan exposure (AUC0-inf) of 24% was observed. This change in zilucoplan exposures is not expected to be clinically significant. No dose adjustment is required in patients with mild or moderate hepatic impairment. The pharmacokinetics of zilucoplan in patients with severe hepatic impairment have not been studied.

Drug Interactions

Clinical drug interaction studies have not been performed with zilucoplan.

In vitro studies have shown that zilucoplan is not a substrate of major cytochrome P450 (CYP) enzymes (1A2, 2B6, 2C8, 2C9, 2C19, 2D6, and 3A) or transporters (P-gp, BCRP, OATP1B1, and OATP1B3). Based on the results from in vitro drug interaction testing, clinically relevant interactions between zilucoplan and substrates of CYP enzymes (1A2, 2B6, 2C8, 2C9, 2C19, 2D6, 3A, and 4F), uridine diphosphoglucuronosyl transferases (UGTs; 1A1, 1A3, 1A4, 1A6, 1A9, 2B7, and 2B15), and transporters (P-gp, BCRP, OATP1B1, OATP1B3, OAT1, OAT3, MATE1, MATE2-K, OCT1, and OCT2) is unlikely.

12.6 Immunogenicity

As with all therapeutic peptides, there is a potential for immunogenicity. The observed incidence of anti-drug antibodies is highly dependent on the sensitivity and specificity of the assay. Differences in assay methods preclude meaningful comparisons of the incidence of anti-drug antibodies in the studies described below with the incidence of anti-drug antibodies in other studies or of other products. The sensitivity of the assay is not known although ADA was detectable in the tested samples.

In up to 12 weeks of treatment in Study 1, 2.3% (2/86) of patients treated with ZILBRYSQ developed anti-drug antibodies (ADA). A total of 9.3% (8/86) of ZILBRYSQ treated patients developed anti-polyethylene glycol (anti-PEG) antibodies. Because of the low occurrence of anti-drug antibodies and anti-PEG antibodies, the available data are too limited to make definitive conclusions regarding immunogenicity and its effect on pharmacokinetics, pharmacodynamics, safety, or efficacy of ZILBRYSQ.

13 NONCLINICAL TOXICOLOGY

13.1 Carcinogenesis, Mutagenesis, Impairment of Fertility

Carcinogenesis

Studies to assess the carcinogenic potential of zilucoplan have not been conducted.

Mutagenesis

Zilucoplan was not genotoxic in in vitro (Ames and chromosomal aberration) and in vivo (rat micronucleus) assays.

Impairment of Fertility

Subcutaneous administration of zilucoplan (0, 1, 2, or 4 mg/kg/day) to male monkeys resulted in testicular germ cell depletion/degeneration at all doses at the end of the 13-week dosing period and after the 8-week recovery period, indicating lack of reversibility.

A no-effect dose for testicular germ cell degeneration was not identified. At the lowest dose tested, plasma exposures (AUC) were similar to that in humans at the maximum recommended human dose of 32.4 mg/day.

14 CLINICAL STUDIES

The efficacy of ZILBRYSQ for the treatment of generalized myasthenia gravis (gMG) in adult patients who are anti-AChR antibody positive was established in a 12-week, multicenter, randomized, double-blind placebo-controlled study (Study 1; NCT04115293).

Study 1 enrolled patients who met the following criteria at screening:

- Myasthenia Gravis Foundation of America (MGFA) clinical classification class II to IV,
- Positive serology for AChR binding autoantibodies,
- MG-Activities of Daily Living (MG-ADL) total score of ≥6,
- Those on MG therapy prior to screening (including acetylcholinesterase (AChE) inhibitors, steroids, or non-steroidal immunosuppressive therapies (NSISTs), either in combination or alone), needed to maintain a stable dose.

A total of 174 patients were enrolled in Study 1 and were randomized 1:1 to receive either ZILBRYSQ 0.3 mg/kg (n=86) or placebo (n=88) once daily by subcutaneous injection. Baseline characteristics were similar between treatment groups. Patients had a mean age of 53.0 years and a mean time since diagnosis of 9 years. Fifty-seven percent of the patients were female, 74% were White, 12% were Asian, 8% were Black, 1% were American Indian or Alaska Native, and 6% did not have race reported. The mean baseline MG-ADL total score was 10.6 (range 6 to 19).

At baseline, approximately 85% of patients in each group received cholinesterase inhibitors, 63% received steroids, and 51% received NSISTs, at stable doses.

The primary efficacy endpoint was a comparison of the change from baseline between treatment groups in the Myasthenia Gravis-Specific Activities of Daily Living scale (MG-ADL) total score after twelve weeks of treatment. The MG-ADL assesses the impact of gMG on daily functions of 8 signs or symptoms that are typically affected in gMG. Each item is assessed on a 4-point scale where a score of 0 represents normal function and a score of 3 represents loss of ability to perform that function. A total score ranges from 0 to 24, with the higher scores indicating more impairment.

The efficacy of ZILBRYSQ was also measured using the Quantitative Myasthenia Gravis (QMG) total score which is a 13-item categorical grading system that assesses muscle weakness. Each item is assessed on a 4-point scale where a score of 0 represents no weakness and a score of 3 represents severe weakness. A total possible score ranges from 0 to 39, where higher scores indicate more severe impairment.

Other secondary endpoints included the proportion of patients with improvements of at least 3 and 5 points in the MG-ADL total score and QMG total score, respectively, at week 12 without rescue therapy.

At week 12, treatment with ZILBRYSQ demonstrated a statistically significant improvement from baseline compared to placebo for MG-ADL total score and QMG total score (Table 3; Figure 1).

Table 3: Change from Baseline in MG-ADL and QMG Total Scores at Week 12 in Adult Patients with gMG who are Anti-AChR Antibody Positive (Study 1)
Efficacy Endpoints: LS Mean (95% CI) | ZILBRYSQ (n = 86) | Placebo (n = 88) | ZILBRYSQ change LS mean difference vs. placebo (95% CI) | p-value*
MG-ADL Total Score | -4.39 (-5.28, -3.50) | -2.30 (-3.17, -1.43) | -2.09 (-3.24, -0.95) | < 0.001
QMG Total Score | -6.19 (-7.29, -5.08) | -3.25 (-4.32, -2.17) | -2.94 (-4.39, -1.49) | < 0.001
Abbreviations: CI = confidence interval; MG-ADL, myasthenia gravis activities of daily living scale; QMG, quantitative myasthenia gravis; LS = least square

Figure 1: Change from Baseline in MG-ADL Total Score (A) and QMG Total Score (B) through Week 12

*Analysis based on MMRM ANCOVA model

The proportion of MG-ADL responders with at least a 3-point improvement at week 12 was greater for ZILBRYSQ (73.1%) compared to placebo (46.1%) (p<0.001). The proportion of QMG responders with at least a 5-point improvement was also greater for ZILBRYSQ (58%) compared to placebo (33%) (p = 0.0012). The proportion of clinical responders at higher response thresholds was consistently greater for ZILBRYSQ compared to placebo.

16 HOW SUPPLIED/STORAGE AND HANDLING

16.1 How Supplied

ZILBRYSQ (zilucoplan) injection prefilled syringe contains a sterile, preservative-free, clear to slightly opalescent, colorless solution. Each single-dose prefilled syringe consists of a 1 mL glass syringe with a 29-gauge ½ inch needle, a needle safety guard, and a needle cover. The ZILBRYSQ prefilled syringe components are not made with natural rubber latex.

ZILBRYSQ is available as follows:

NDC | Carton Pack Size | Strength | Plunger Color
50474-990-80 | 28 single-dose prefilled syringes (4 cartons each containing 7 syringes for a total of 28 syringes) | 16.6 mg/0.416 mL | RUBINE RED
50474-991-80 | 28 single-dose prefilled syringes (4 cartons each containing 7 syringes for a total of 28 syringes) | 23 mg/0.574 mL | ORANGE
50474-992-80 | 28 single-dose prefilled syringes (4 cartons each containing 7 syringes for a total of 28 syringes) | 32.4 mg/0.81 mL | DARK BLUE

16.2 Storage and Handling

Pharmacy Prior to Dispensing

Store ZILBRYSQ prefilled syringes refrigerated at 2°C to 8°C (36°F to 46°F) in the original carton until dispensing. Do not freeze.

Storage for Patients or Caregivers After Dispensing

Storage conditions after dispensing by pharmacist are summarized in Table 4:

Table 4: After Dispensing Storage Conditions
Temperature | Refrigeration 2°C to 8°C (36°F to 46°F) | Room Temperature Up to 30°C (86°F)
Time Period | Until expiration date on the carton | Up to 3 months after removing from refrigerator or until expiration date on the carton, whichever occurs first

- Do not freeze.
- Store ZILBRYSQ prefilled syringes in the original carton to protect them from light until time of use.
- ZILBRYSQ prefilled syringes may be stored at room temperature in the original carton for a single period of up to 3 months.
  - When storing ZILBRYSQ prefilled syringes at room temperature, write the date removed from the refrigerator in the space provided on the carton and discard if not used within 3 months or if the expiration date has passed, whichever occurs first.
  - Do not return ZILBRYSQ to the refrigerator after it has been stored at room temperature.
- ZILBRYSQ does not contain a preservative; discard any unused portion.

17 PATIENT COUNSELING INFORMATION

Advise the patients and/or caregivers to read FDA-approved patient labeling (Medication Guide and Instructions for Use) .

Serious Meningococcal Infection

Advise patients of the risk of serious meningococcal infection [see Warnings and Precautions (5.1)] . Inform patients of the need to complete or update meningococcal vaccinations at least 2 weeks prior to receiving the first dose of ZILBRYSQ or receive antibacterial drug prophylaxis if ZILBRYSQ treatment must be initiated immediately and they have not been previously vaccinated. Inform patients of the requirement to be revaccinated according to current ACIP recommendations for meningococcal infection while on ZILBRYSQ therapy.

Inform patients that vaccination may not prevent serious meningococcal infection and to seek immediate medical attention if the following signs or symptoms occur:

- fever
- fever and a rash
- fever with high heart rate
- headache with nausea or vomiting
- headache and a fever
- headache with a stiff neck or stiff back
- confusion
- muscle aches with flu-like symptoms
- eyes sensitive to light

Inform patients that they will be given a Patient Safety Card for ZILBRYSQ that they should carry with them at all times and for 2 months following treatment with ZILBRYSQ. This card describes symptoms which, if experienced, should prompt the patient to immediately seek medical evaluation.

ZILBRYSQ REMS

ZILBRYSQ is available only through a restricted program called ZILBRYSQ REMS [see Warnings and Precautions (5.2)].

Inform the patient of the following notable requirements:

- Patients must receive counseling about the risk of serious meningococcal infections.
- Patients must receive written educational materials about this risk.
- Patients must be instructed to carry the Patient Safety Card with them at all times during and for 2 months following treatment with ZILBRYSQ.
- Patients must be instructed to complete or update meningococcal vaccines for serogroups A, C, W, Y, and B per ACIP recommendations as directed by the prescriber prior to treatment with ZILBRYSQ.
- Patients must receive antibiotics as directed by the prescriber if they are not up to date with meningococcal vaccines and have to start ZILBRYSQ right away.

Other Infections

Counsel patients of the increased risk of infections, particularly those due to encapsulated bacteria, especially Neisseriaspecies. Advise patients of the need for vaccination against meningococcal infections according to current medical guidelines [see Warnings and Precautions (5.3)] . Counsel patients about gonorrhea prevention and advise regular testing for patients at risk. Advise patients to report any new signs and symptoms of infection.

Pancreatitis and Other Pancreatic Conditions

Inform patients that pancreatitis and pancreatic cysts have been reported in patients taking ZILBRYSQ. Inform patients that persistent abdominal pain, sometimes severe or radiating to the back, which may or may not be accompanied by vomiting, is the hallmark symptom of acute pancreatitis. Instruct patients to contact their healthcare provider if these symptoms occur to determine if they should discontinue ZILBRYSQ [see Warnings and Precautions (5.4)] .

Pregnancy Registry

Advise patients that there is registry that monitors outcomes in patients with Myasthenia Gravis, including women exposed to ZILBRYSQ during pregnancy and/or breastfeeding [see Use in Specific Populations (8.1)].

Administration

Provide training to patients and caregivers on proper subcutaneous injection technique.

Instruct patients to inject the full dose of ZILBRYSQ [see Medication Guideand Instructions for Use] .

Instruct patients or caregivers in the technique of needle and syringe disposal [see Instructions for Use].

Remind patients if they forget to take their dose of ZILBRYSQ to inject their dose as soon as they remember. They should then take their next dose at the appropriate scheduled time. They should not take more than 1 dose per day.

Manufactured for:
UCB, Inc.
1950 Lake Park Drive
Smyrna, GA 30080

ZILBRYSQ®is a registered trademark of the UCB Group of Companies.
©2025 UCB, Inc., Smyrna, GA 30080. All rights reserved.

MEDICATION GUIDE
ZILBRYSQ®(ZIL-brisk)
(zilucoplan)
injection, for subcutaneous use

What is the most important information I should know about ZILBRYSQ?
ZILBRYSQ is a medicine that affects part of your immune system. ZILBRYSQ may lower the ability of your immune system to fight infections.

- ZILBRYSQ increases your chance of getting serious meningococcal infections caused by Neisseria meningitidisbacteria. Meningococcal infections may quickly become life-threatening or cause death if not recognized and treated early.
  - You must complete or update your meningococcal vaccine(s) at least 2 weeks before your first dose of ZILBRYSQ.
  - If you have not completed your meningococcal vaccines and ZILBRYSQ must be started right away, you should receive the required vaccine(s) as soon as possible.
  - If you have not been vaccinated and ZILBRYSQ must be started right away, you should also receive antibiotics to take for as long as your healthcare provider tells you.
  - If you had a meningococcal vaccine in the past, you might need additional vaccines before starting ZILBRYSQ. Your healthcare provider will decide if you need additional meningococcal vaccines.
  - Meningococcal vaccines do not prevent all meningococcal infections. Call your healthcare provider or get emergency medical care right away if you get any of these signs and symptoms of a meningococcal infection:

- fever
- fever with high heart rate
- headache and fever
- confusion
- muscle aches with flu-like symptoms

- fever and a rash
- headache with nausea or vomiting
- headache with a stiff neck or stiff back
- eyes sensitive to light

Your healthcare provider will give you a Patient Safety Card about the risk of serious meningococcal infection.Carry it with you at all times during treatment and for 2 months after your last ZILBRYSQ dose. Your risk of meningococcal infection may continue for several weeks after your last dose of ZILBRYSQ. It is important to show this card to any healthcare provider who treats you. This will help them diagnose and treat you quickly.
ZILBRYSQ is only available through a program called the ZILBRYSQ Risk Evaluation and Mitigation Strategy (REMS).Before you can receive ZILBRYSQ, your healthcare provider must:

- enroll in the ZILBRYSQ REMS program.
- counsel you about the risk of meningococcal infections.
- give you the Patient Guide, including information about the signs and symptoms of meningococcal infection.
- give you a Patient Safety Cardabout your risk of meningococcal infection, as discussed above.
- make sure that you are vaccinated against serious infections caused by meningococcal bacteria and that you receive antibiotics if you need to start ZILBRYSQ right away and you are not up to date on your vaccines.

ZILBRYSQ may also increase the risk of other types of serious infectionscaused by encapsulated bacteria, including Streptococcus pneumoniae, Haemophilus influenzae, and Neisseria gonorrhoeae.

- Certain people may be at risk of serious infections with gonorrhea. Talk to your healthcare provider about whether you are at risk for gonorrhea infection, about gonorrhea prevention, and about regular testing.

Call your healthcare provider right away if you have new signs or symptoms of infection.

What is ZILBRYSQ?

- ZILBRYSQ is a prescription medicine used to treat adults with a disease called generalized myasthenia gravis (gMG) who are anti-acetylcholine receptor (AChR) antibody positive.
- It is not known if ZILBRYSQ is safe and effective in children.

Who should not use ZILBRYSQ?

- Do not use ZILBRYSQ if youhave a serious meningococcal infection when you are starting ZILBRYSQ treatment.

Before you use ZILBRYSQ, tell your healthcare provider about all of your medical conditions, including if you:

- have an infection or fever.
- are pregnant or plan to become pregnant. It is not known if ZILBRYSQ will harm your unborn baby.
  - There is a pregnancy registry for women who use ZILBRYSQ during pregnancy. The purpose of this registry is to collect information about the health of you and your baby. If you become pregnant while taking ZILBRYSQ, you or your healthcare provider can contact UCBCares at 1-844-599-CARE (2273) or email ucbcares@ucb.com, to enroll or get more information about the registry.
- are breastfeeding or plan to breastfeed. It is not known if ZILBRYSQ passes into your breast milk. Talk to your healthcare provider about the best way to feed your baby if you use ZILBRYSQ.

Tell your healthcare provider about all the medicines you take,including prescription and over-the-counter medicines, vitamins, and herbal supplements.
Know the medicines you take and the vaccines you receive. Keep a list of them to show your healthcare provider and pharmacist when you get a new medicine.

How should I use ZILBRYSQ?
See the detailed Instructions for Usethat comes with your ZILBRYSQ for information on how to prepare and inject a dose of ZILBRYSQ, and how to properly throw away (dispose of) used ZILBRYSQ prefilled syringes.

- ZILBRYSQ is given as an injection under the skin (for subcutaneous use) in a prefilled syringe. Use ZILBRYSQ exactly as prescribed by your healthcare provider.
- After proper training on how to prepare and inject your ZILBRYSQ syringe, you or your caregiver will inject ZILBRYSQ daily. Your healthcare provider will decide the total daily dose depending on your body weight.
- Each prefilled syringe is for single-use only. Throw away the prefilled syringe after each use. Do not reuse.
- Your daily dose of ZILBRYSQ should be injected at about the same time each day.

If you miss your ZILBRYSQ dose, inject a dose as soon as possible. Then, inject your next dose at your regular scheduled time. Do not inject more than 1 dose each day. Call your healthcare provider if you are not sure what to do.

What are the possible side effects of ZILBRYSQ?
ZILBRYSQ may cause serious side effects, including:

- See " What is the most important information I should know about ZILBRYSQ?"
- Inflammation of the pancreas (pancreatitis) and other pancreatic problems.Pancreatitis and pancreatic cysts have happened in people who use ZILBRYSQ. Your healthcare provider will do blood tests to check your pancreas before you start treatment with ZILBRYSQ.
  - Call your healthcare provider right awayif you have pain in your stomach area (abdomen) that will not go away. Your healthcare provider will tell you if you should stop using ZILBRYSQ. The pain may be severe or felt going from your abdomen to your back. The pain may happen with or without vomiting. These may be symptoms of pancreatitis.

The most common side effects of ZILBRYSQ include:

- injection site reactions.
- upper respiratory tract infections.
- diarrhea.

Tell your healthcare provider about any side effect that bothers you or that does not go away.
These are not all the possible side effects of ZILBRYSQ.
Call your doctor for medical advice about side effects. You may report side effects to FDA at 1-800-FDA-1088.

How should I store ZILBRYSQ?

- ZILBRYSQ prefilled syringes may be stored in the refrigerator between 36°F to 46°F (2°C to 8°C) until the expiration date on the carton. Do not freeze ZILBRYSQ. Keep the prefilled syringes in the original carton until ready for use to protect from light.
- ZILBRYSQ prefilled syringes may be stored at room temperature up to 86°F (30°C) in the original carton to protect them from light for a single period of up to 3 months. Write the date you removed the prefilled syringes from the refrigerator in the space provided on the carton. After ZILBRYSQ prefilled syringes have been stored at room temperature, do not place them back in the refrigerator and throw them away if not used within the 3-month period or if the expiration date has passed, whichever occurs first.
- Throw away any unused portion.

Keep ZILBRYSQ prefilled syringes and all medicines out of the reach of children.

General information about the safe and effective use of ZILBRYSQ.
Medicines are sometimes prescribed for purposes other than those listed in a Medication Guide. Do not use ZILBRYSQ for a condition for which it was not prescribed. Do not give ZILBRYSQ to other people, even if they have the same symptoms that you have. It may harm them. You can ask your pharmacist or healthcare provider for information about ZILBRYSQ that is written for health professionals.

What are the ingredients in ZILBRYSQ?
Active ingredient:zilucoplan
Inactive ingredients:dibasic sodium phosphate, anhydrous, monobasic sodium phosphate, monohydrate, sodium chloride, and water for injection.
Manufactured for UCB, Inc., Smyrna, GA 30080
ZILBRYSQ®is a registered trademark of the UCB Group of Companies.
©2025 UCB, Inc., Smyrna, GA 30080.
All rights reserved.
For more information, visit www.ZILBRYSQ.com or call 1-844-599-2273.

This Medication Guide has been approved by the U.S. Food and Drug Administration.

Issued: 1/2026

INSTRUCTIONS FOR USE

ZILBRYSQ®(ZIL-brisk)
(zilucoplan)
injection, for subcutaneous use
Single-Dose Prefilled Syringe

This Instructions for Use contains information on how to inject ZILBRYSQ.

Understanding Your ZILBRYSQ Prefilled Syringe

Read this Instructions for Use before using the ZILBRYSQ prefilled syringe. This information does not take the place of talking to your healthcare provider about your medical condition or treatment. See the Medication Guidethat comes with ZILBRYSQ for important information.

Your healthcare provider should show you how to prepare and inject ZILBRYSQ prefilled syringe properly before you use it for the first time. Do not inject yourself or someone else until you have been shown how to inject ZILBRYSQ correctly.

Keep this Instructions for Use and refer to it as needed until you have used all of the ZILBRYSQ prefilled syringes in the packaging.

For general questions or help, please call your healthcare provider or UCBCares at 1-844-599-CARE (2273).

How Should I Store ZILBRYSQ Prefilled Syringes?

- Store ZILBRYSQ prefilled syringes in a refrigerator between 36°F to 46°F (2°C to 8°C) until the expiration date on the carton. Do not freeze ZILBRYSQ.
- ZILBRYSQ prefilled syringes may be stored at room temperature up to 86°F (30°C) in the original carton for a single period of up to 3 months. Write the date you removed the prefilled syringes from the refrigerator in the space provided on the carton. After ZILBRYSQ prefilled syringes have been stored at room temperature, do not place them back in the refrigerator. Throw them away if not used within 3 months or if the expiration date has passed, whichever occurs first.
- Keep the ZILBRYSQ prefilled syringes in the original carton before use.
- Keep ZILBRYSQ prefilled syringes and all medicines out of the reach of children.

Important Information You Need to Know Before You Inject ZILBRYSQ

- Do notuse ZILBRYSQ if the expiration date on the packaging has passed or the carton seals have been broken.
- Do notreuse the ZILBRYSQ prefilled syringe. The prefilled syringe is for 1-time (single use) only. You may get an infection.
- Do notinject ZILBRYSQ more than 1 time per day.
- Do notmiss any doses of ZILBRYSQ. If you miss your ZILBRYSQ dose, inject a dose as soon as possible. Then, inject the next dose at your scheduled time. Do not inject more than 1 dose each day.
- Do notuse the ZILBRYSQ prefilled syringe if it has been dropped.
- Do notremove the needle cap from the ZILBRYSQ prefilled syringe until you are ready to inject.
- Do notinsert the needle into the skin more than 1 time because this may bend or break the needle, causing trauma to the tissue.
- Do notpull back on the ZILBRYSQ prefilled syringe plunger head at any time because this can break the prefilled syringe.
- Do nottouch the needle guard activation clips at any time because this can cause the early activation of the needle guard.

ZILBRYSQ Prefilled Syringe Guide to Parts (Figure A):

Before use

After use

Figure A

Preparing for Injection

Step 1: Take out the ZILBRYSQ prefilled syringe

If the ZILBRYSQ prefilled syringes are stored in the refrigerator:

- Take the ZILBRYSQ prefilled syringes carton out of the refrigerator and remove 1 prefilled syringe from the carton. Grasp the prefilled syringe body.Carefully lift the prefilled syringe straight up out of the tray (Figures B.1 and B.2). Put the rest of the prefilled syringes in the carton back in the refrigerator.
- Before you inject ZILBRYSQ, let the prefilled syringe warm up to room temperature on a clean flat surface for 30 to 45 minutes. This will help to reduce discomfort when injecting.
- Do not warm the ZILBRYSQ prefilled syringe in any other way (for example in a microwave, in hot water, or in direct sunlight).
- Do not remove the needle cap from the prefilled syringe until you are ready to inject.

If the ZILBRYSQ prefilled syringes are stored at room temperature:

- Remove 1 ZILBRYSQ prefilled syringe from the carton. Grasp the prefilled syringe body.Carefully lift the prefilled syringe straight up out of the tray (Figures B.1 and B.2). Any remaining prefilled syringes in the carton should not be placed in the refrigerator after it has been stored at room temperature.

Figure B.1

Figure B.2

Step 2: Inspect the ZILBRYSQ prefilled syringe

- Check the prefilled syringe for damage (Figure C).
- Do notuse if any part of the prefilled syringe appears to be cracked, leaking, or broken.
- Check thatthe needle cap is not cracked or broken and attached to the prefilled syringe (Figure C).
- Do notuse if the needle cap is missing or not securely attached.
- Check the expiration date and medicine name (ZILBRYSQ) on the prefilled syringe label (Figure C).
- Do notuse if the expiration date printed on the prefilled syringe has passed.
- Do notuse if the word ZILBRYSQ does not appear on the prefilled syringe.
- Check the dose appearing on the label (Figure C)and make sure it matches your prescribed dose.
- Do notuse if the dose does not match your prescribed dose.
- Check the medicine inside the prefilled syringe (Figure C). The medicine should be clear to almost clear and colorless. It is normal to see air bubbles in the prefilled syringe.
- Do notuse if the medicine is cloudy, discolored, or contains floating particles.
  Figure C

Step 3: Gather supplies

Wash your hands with soap and water and dry them with a clean towel.

Gather the following supplies on a clean, flat surface (Figure D):

- 1 ZILBRYSQ prefilled syringe
- 1 alcohol wipe (not supplied)
- 1 cotton ball or gauze pad (not supplied)
- 1 adhesive bandage (not supplied)
- 1 sharps disposal or puncture-resistant container (not supplied). See Step 12for instructions on throwing away the syringe.
  Figure D

Step 4: Choose your injection site

Choose an injection site from the following areas (Figures E.1 and E.2):

- The stomach (abdomen), except for the 2-inch area around the belly button (navel) (Figure E.1)
- The front of the thighs (Figure E.1)
  Figure E.1 – abdomen and thighs
- The back of the upper arms (only if someone else is giving you the injection) (Figure E.2)
  Figure E.2 – upper arms

Choose a different site each time you give yourself an injection. If you want to use the same injection site, make sure it is at least 1-inch from a spot you used before.

Do notinject ZILBRYSQ into an area that is red, tender, bruised, swollen, hard or that has scars or stretch marks.

Step 5: Clean your injection site

Clean the injection site using an alcohol wipe (Figure F).

Let the skin dry for 10 seconds before injecting.

Do nottouch the injection site again before giving your injection.

Figure F

Injecting the Medicine

Step 6: Remove the needle cap

Hold the body of the ZILBRYSQ prefilled syringe with one hand and pull the needle cap straight off with your other hand (Figure G).

Figure G

Throw away (discard) the needle cap into your household trash or a sharps disposal container.

Do nottouch the needle or let it touch anything.

Do notrecap the needle at any time to avoid injury.

Do nottry to remove any air bubbles from the ZILBRYSQ prefilled syringe. Air bubbles will not affect your dose and will not harm you. This is normal. You can continue to take your injection.

Step 7: Pinch your injection site

Use your other hand to pinch the area of cleaned skin and hold it firmly (Figure H).

Figure H

Step 8: Insert the needle

Insert the entire needle into the pinched skin at a 45° to 90° angle. When the needle is fully inserted, hold the ZILBRYSQ prefilled syringe in place (Figure I).

Do notpull back on the plunger head at any time because this could break the prefilled syringe.

Do nottouch the needle guard activation clips.

Figure I

Step 9: Release the pinched skin

When the needle is fully inserted, hold the ZILBRYSQ prefilled syringe in place and release the pinched skin (Figure J).

Figure J

Do notreinsert the needle into the skin if the needle is pulled out when releasing the skin. If this happens, safely throw away (dispose of) the syringe in a sharps disposal container and get a new ZILBRYSQ prefilled syringe to give the injection.

Step 10: Inject the medicine

Push the plunger head all the way down while holding onto the finger grip to inject all the medicine (Figure K).

Figure K

Step 11: Release the plunger head

Slowly release the plunger head by lifting your thumb. After a complete injection, the needle guard will cover the needle and you may hear a click (Figure L).

Figure L

Step 12: Throw away (dispose of) the used ZILBRYSQ prefilled syringe

Throw away (dispose of) the used ZILBRYSQ prefilled syringe into a sharps disposal container (Figure M)right away.

Do notthrow away (dispose of) the ZILBRYSQ prefilled syringe in your household trash.

If you do not have an FDA-cleared sharps disposal container, you may use a household container that is:

- made of a heavy-duty plastic,
- can be closed with a tight-fitting, puncture-resistant lid, without sharps being able to come out,
- upright and stable during use,
- leak-resistant, and
- properly labelled to warn of hazardous waste inside the container.

Do notthrow away (dispose of) your used sharps disposal container in your household trash unless your community guidelines permit this.

Do notrecycle your used sharps disposal container.

Always keep the sharps disposal container out of the reach of children.

Note:When your sharps disposal container is almost full, you will need to follow your community guidelines for the right way to dispose of your sharps disposal container. There may be state or local laws about how you should throw away your used needles and syringes. For more information about safe sharps disposal, and for specific information about sharps disposal in the state you live in, go to the FDA's website at: http://www.fda.gov/safesharpsdisposal.

Figure M

Step 13: Examine the injection site

Press a cotton ball or gauze pad over the injection site and hold it for 10 seconds (Figure N).

Do notrub the injection site. You may have slight bleeding. This is normal. Apply an adhesive bandage if needed (Figure O).

Figure N

Figure O

The injection is complete.

For more information or help, contact your healthcare provider.

If you have any questions, call UCBCares at 1-844-599-CARE (2273) or visit www.AskUCBCares.com.

Manufactured for:
UCB, Inc.
Smyrna, GA 30080

This Instructions for Use has been approved by the U.S. Food and Drug Administration.
Issued: 10/2023

PRINCIPAL DISPLAY PANEL - 16.6 mg/0.416 mL Syringe Carton Box

NDC 50474-990-80
Rx only

Do not accept
if seal is missing or broken.

Lift here to open. ⇾

ZILBRYSQ®
(zilucoplan) Injection
16.6 mg/0.416 mL
For Subcutaneous Use Only

28
Single-Dose Prefilled Syringes
Affixed with an automatic needle
protection system

This carton contains 4 individual cartons.
The entire carton is to be dispensed as one unit.

ONCE DAILY
ATTENTION PHARMACIST: Dispense the enclosed
Medication Guide to each patient.

Each individual carton contains: 7 Single-Dose
Prefilled Syringes.

PRINCIPAL DISPLAY PANEL - 23 mg/0.574 mL Syringe Carton Box

NDC 50474-991-80
Rx only

Do not accept
if seal is missing or broken.

Lift here to open. ⇾

ZILBRYSQ®
(zilucoplan) Injection
23 mg/0.574 mL
For Subcutaneous Use Only

28
Single-Dose Prefilled Syringes
Affixed with an automatic needle
protection system

This carton contains 4 individual cartons.
The entire carton is to be dispensed as one unit.

ONCE DAILY
ATTENTION PHARMACIST: Dispense the enclosed
Medication Guide to each patient.

Each individual carton contains: 7 Single-Dose
Prefilled Syringes.

PRINCIPAL DISPLAY PANEL - 32.4 mg/0.81 mL Syringe Carton Box

NDC 50474-992-80
Rx only

Do not accept
if seal is missing or broken.

Lift here to open. ⇾

ZILBRYSQ®
(zilucoplan) Injection
32.4 mg/0.81 mL
For Subcutaneous Use Only

28
Single-Dose Prefilled Syringes
Affixed with an automatic needle
protection system

This carton contains 4 individual cartons.
The entire carton is to be dispensed as one unit.

ONCE DAILY
ATTENTION PHARMACIST: Dispense the enclosed
Medication Guide to each patient.

Each individual carton contains: 7 Single-Dose
Prefilled Syringes.